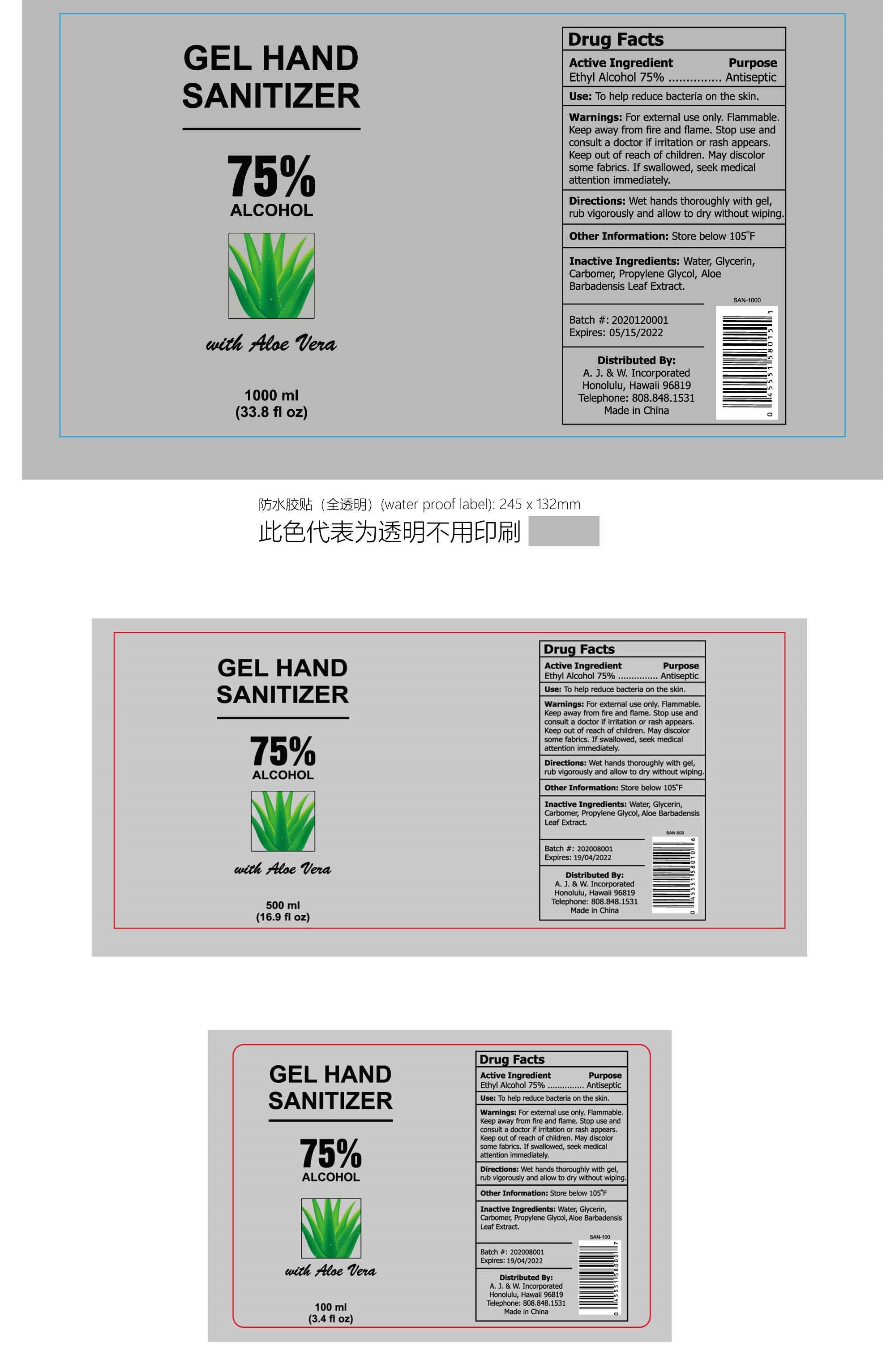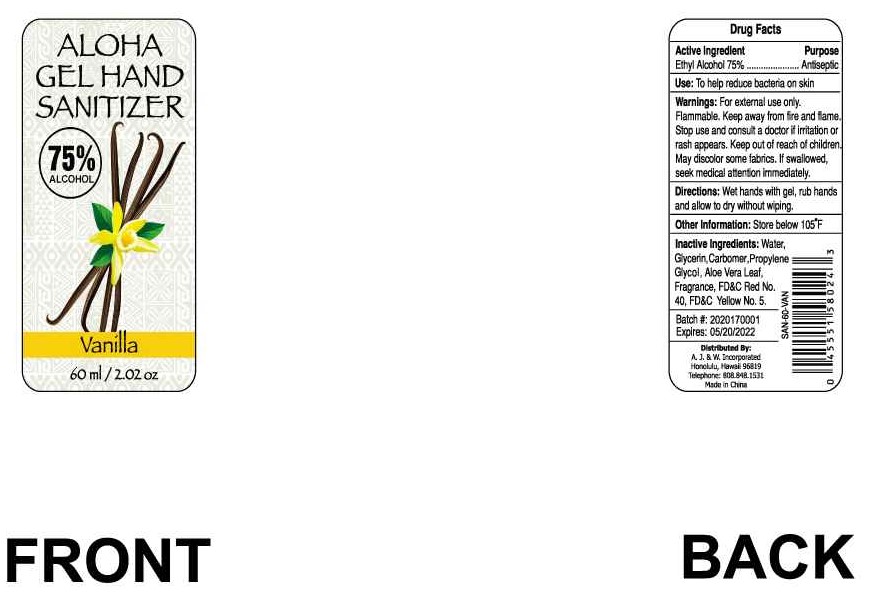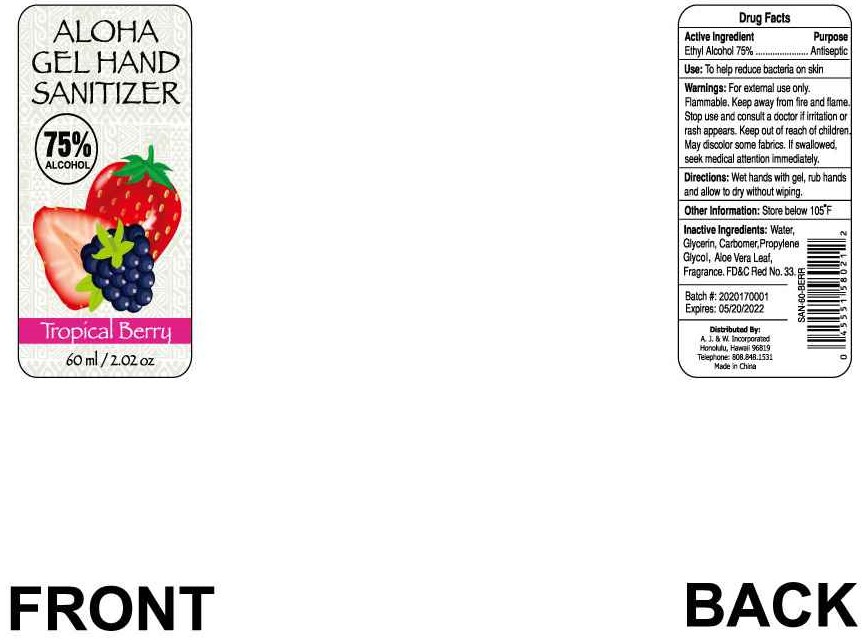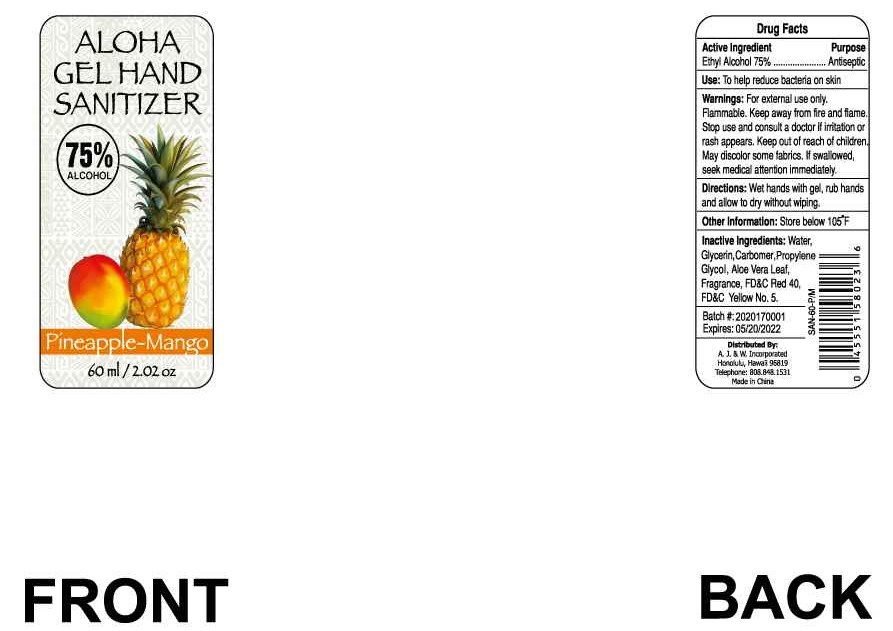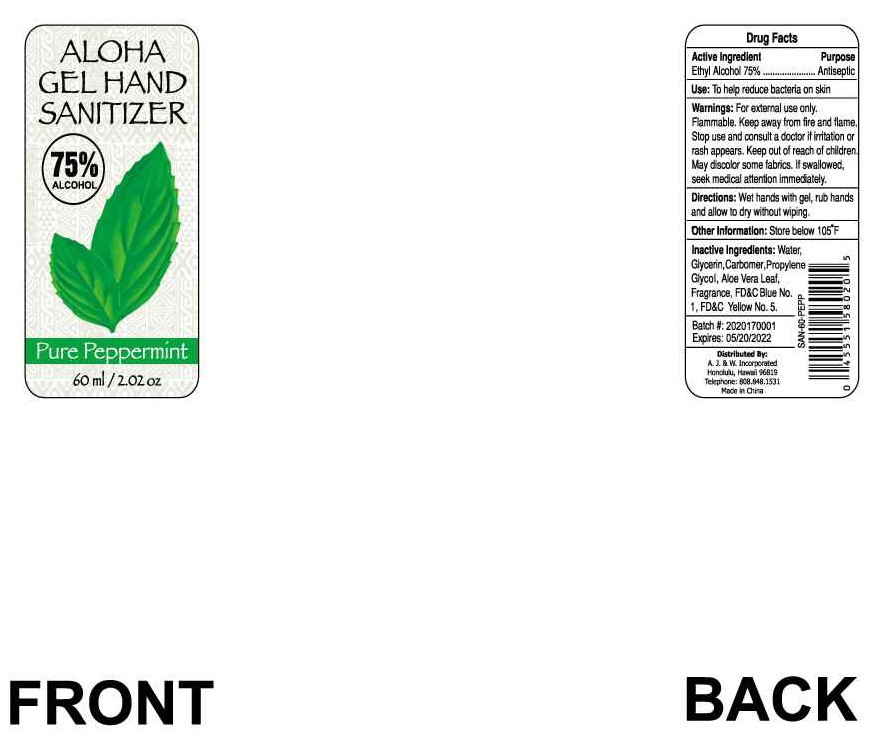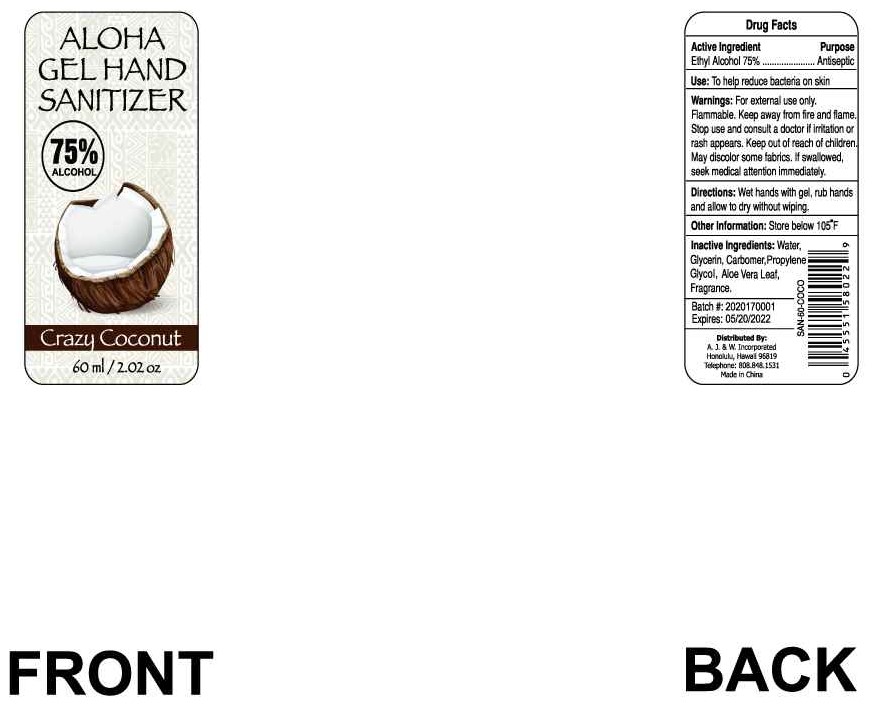 DRUG LABEL: Aloha Gel Hand Sanitizer Pineapple-Mango
NDC: 74657-013 | Form: GEL
Manufacturer: Double Body Biotech Limited
Category: otc | Type: HUMAN OTC DRUG LABEL
Date: 20200615

ACTIVE INGREDIENTS: ALCOHOL 75 mL/100 mL
INACTIVE INGREDIENTS: FD&C RED NO. 40; PROPYLENE GLYCOL; ALOE VERA LEAF; CARBOMER 980; WATER; GLYCERIN; FD&C YELLOW NO. 5

Double Body Aloha Gel Hand Sanitizer

ACTIVE INGREDIENT

Ethyl Alcohol 75%

Purpose

Antiseptic

Uses

Hand Sanitizer to help reduce bacteria that potentially can cause disease. For use when soap and water are not available.

Warnings

For external use only.

Flammable, keep away from fire and flame.

Stop use and consult a doctor if irritation or rash appears.

Keep out of reach of children.

DO NOT USE

If swallowed, seek medical attention immediately.

Directions

Wet hands thoroughly with gel, rub vigorously and allow to dry without wiping.

Other information

Store below 105°F

may discolor certain fabrics

Inactive Ingredient:

(only for Package NDC: 74657-010-01; 74657-010-05; 74657-010-10)*

Water, Glycerin, Carbomer, Propylene Glycol, Aloe Barbadensis Leaf Extract.

(only for Package NDC: 74657-011-01)*

Water, Glycerin, Carbomer, Propylene Glycol, Aloe Vera Leaf, Frangrance, FD&C Red No. 40, FD&C Yellow No. 5.

(only for Package NDC: 74657-012-01)*

Water, Glycerin, Carbomer, Propylene Glycol, Aloe Vera Leaf, Frangrance, FD&C Red No. 33.

(only for Package NDC: 74657-013-01)*

Water, Glycerin, Carbomer, Propylene Glycol, Aloe Vera Leaf, Frangrance, FD&C Red 40, FD&C Yellow No. 5.

(only for Package NDC: 74657-014-01)*

Water, Glycerin, Carbomer, Propylene Glycol, Aloe Vera Leaf, Frangrance, FD&C Blue No. 1, FD&C Yellow No. 5.

(only for Package NDC: 74657-015-01)*

Water, Glycerin, Carbomer, Propylene Glycol, Aloe Vera Leaf, Frangrance

*Remark: , All words in the brackets are not shown on the labels.

PACKAGE LABEL

1000ml, Package NDC: 74657-010-10; 500ml, Package NDC: 74657-010-05; 100ml, Package NDC: 74657-010-01; 60ml, Product NDC: 74657-011-01; 60ml, Product NDC: 74657-012-01; 60ml, Product NDC: 74657-013-01; 60ml, Product NDC: 74657-013-01; 60ml, Product NDC: 74657-014-01; 60ml, Product NDC: 74657-015-01